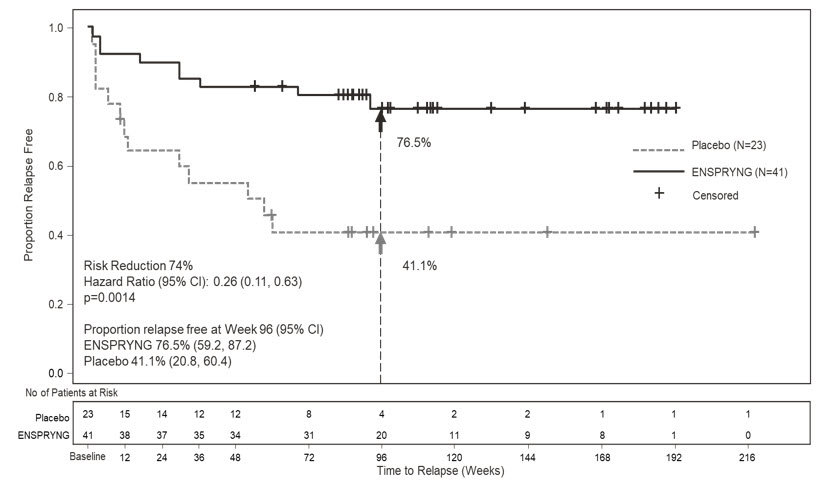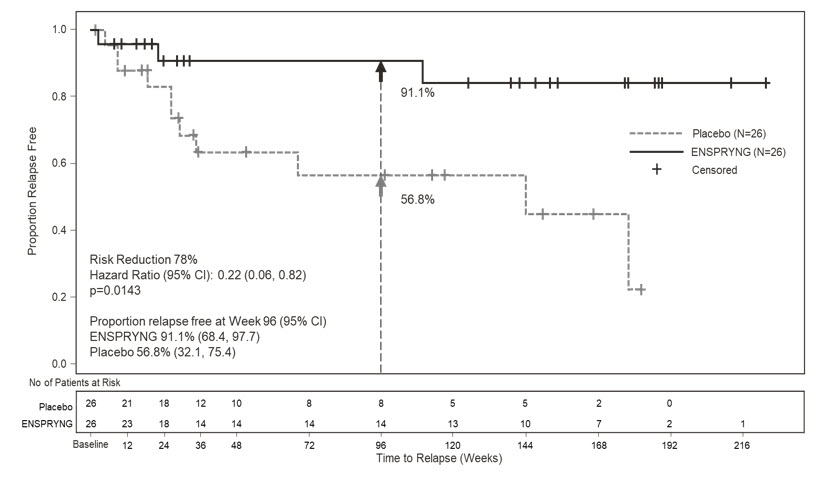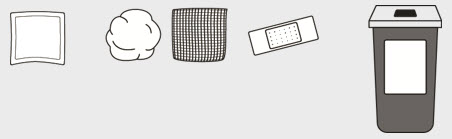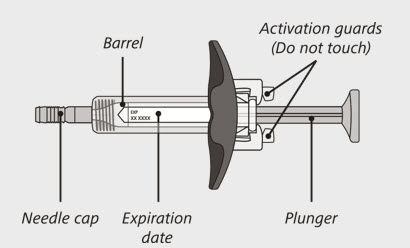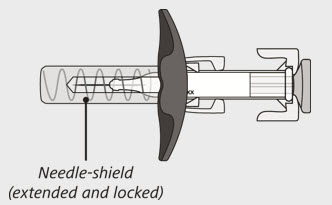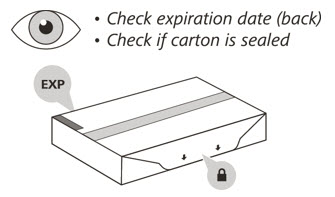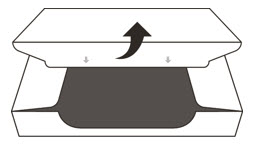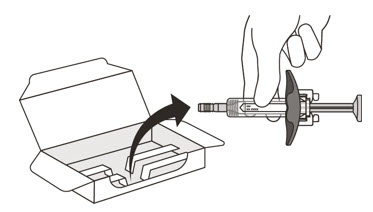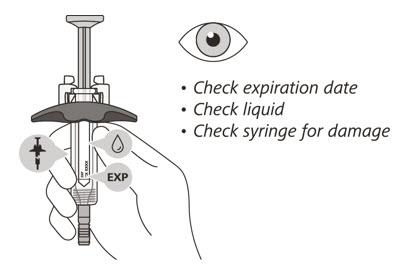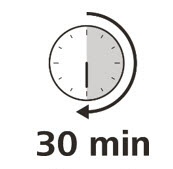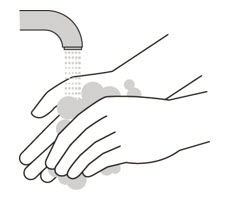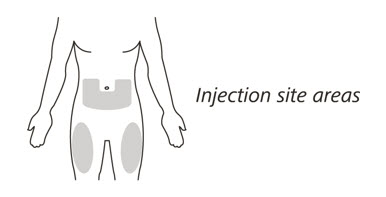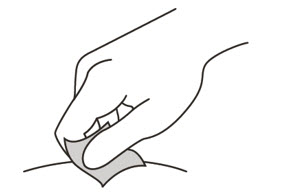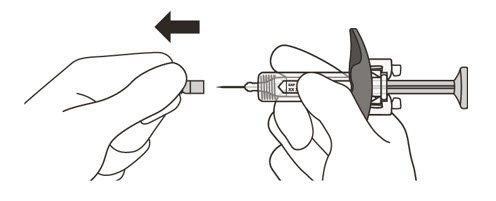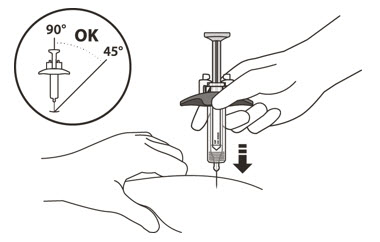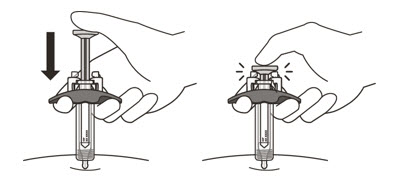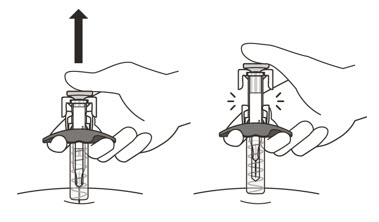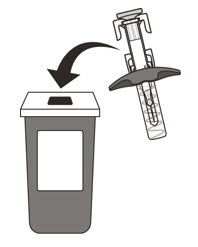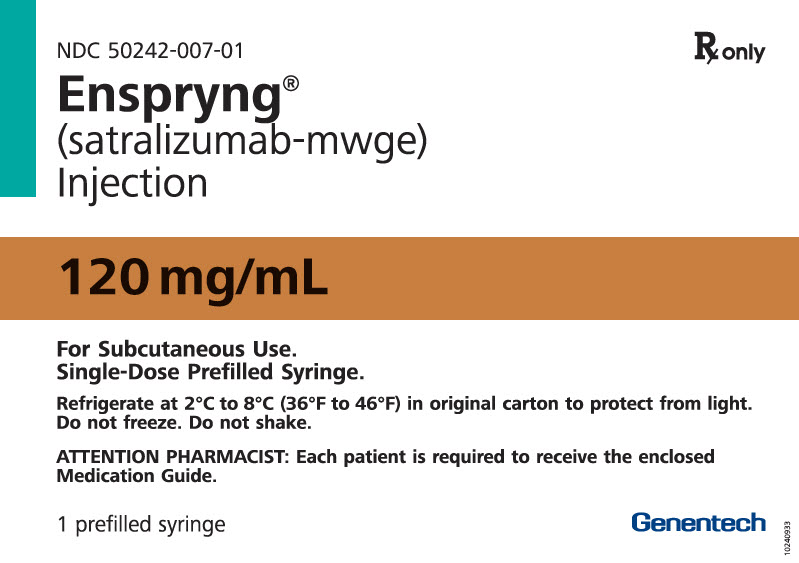 DRUG LABEL: Enspryng
NDC: 50242-007 | Form: INJECTION, SOLUTION
Manufacturer: Genentech, Inc.
Category: prescription | Type: HUMAN PRESCRIPTION DRUG LABEL
Date: 20251203

ACTIVE INGREDIENTS: SATRALIZUMAB 120 mg/1 mL
INACTIVE INGREDIENTS: HISTIDINE 3.1 mg/1 mL; ASPARTIC ACID; ARGININE 26.1 mg/1 mL; POLOXAMER 188 0.5 mg/1 mL; WATER

HIGHLIGHTS OF PRESCRIBING INFORMATION

These highlights do not include all the information needed to use ENSPRYNG safely and effectively. See full prescribing information for ENSPRYNG.
ENSPRYNG® (satralizumab-mwge) injection, for subcutaneous use
Initial U.S. Approval: 2020

1 INDICATIONS AND USAGE

ENSPRYNG is an interleukin-6 (IL-6) receptor antagonist indicated for the treatment of neuromyelitis optica spectrum disorder (NMOSD) in adult patients who are anti-aquaporin-4 (AQP4) antibody positive. (1)

2 DOSAGE AND ADMINISTRATION

- Hepatitis B virus, tuberculosis, and liver transaminase screening is required before the first dose. (2.1)
- Prior to every use, determine if there is an active infection. (2.2)
- The recommended loading dosage of ENSPRYNG for the first three administrations is 120 mg by subcutaneous injection at Weeks 0, 2, and 4, followed by a maintenance dosage of 120 mg every 4 weeks. (2.2)
- See Full Prescribing Information for important preparation and administration instructions. (2.3)

3 DOSAGE FORMS AND STRENGTHS

Injection: 120 mg/mL in a single-dose prefilled syringe (3)

4 CONTRAINDICATIONS

- Known hypersensitivity to satralizumab or any of the inactive ingredients (4)
- Active Hepatitis B infection (4)
- Active or untreated latent tuberculosis (4)

5 WARNINGS AND PRECAUTIONS

- Infections: Delay ENSPRYNG administration in patients with an active infection until the infection is resolved. Vaccination with live or live-attenuated vaccines is not recommended during treatment. (5.1)
- Elevated Liver Enzymes: Monitor ALT and AST levels during treatment; interruption of ENSPRYNG may be required. (5.2)
- Decreased Neutrophil Counts: Monitor neutrophils during treatment. (5.3)

6 ADVERSE REACTIONS

The most common adverse reactions (incidence at least 15%) are nasopharyngitis, headache, upper respiratory tract infection, gastritis, rash, arthralgia, extremity pain, fatigue, and nausea. (6.1)

To report SUSPECTED ADVERSE REACTIONS, contact Genentech at 1-888-835-2555 or FDA at 1-800-FDA-1088 or www.fda.gov/medwatch.

FULL PRESCRIBING INFORMATION

1 INDICATIONS AND USAGE

ENSPRYNG is indicated for the treatment of neuromyelitis optica spectrum disorder (NMOSD) in adult patients who are anti-aquaporin-4 (AQP4) antibody positive.

2 DOSAGE AND ADMINISTRATION

2.1 Assessments Prior to the First Dose of ENSPRYNG

Hepatitis B Virus Screening

Prior to initiating ENSPRYNG, perform Hepatitis B virus (HBV) screening. ENSPRYNG is contraindicated in patients with active HBV confirmed by positive results for surface antigen [HBsAg] and anti-HBV tests. For patients who are negative for HBsAg and positive for HB core antibody [HBcAb+] or are carriers of HBV [HBsAg+], consult liver disease experts before starting and during treatment with ENSPRYNG [see Contraindications (4) and Warnings and Precautions (5.1)].

Tuberculosis Screening

Prior to initiating ENSPRYNG, evaluate for active tuberculosis and test for latent infection. For patients with active tuberculosis or positive tuberculosis screening without a history of appropriate treatment, consult infectious disease experts before initiating treatment with ENSPRYNG [see Contraindications (4) and Warnings and Precautions (5.1)].

Liver Transaminase Screening

Liver transaminases and serum bilirubin should be assessed prior to initiation of treatment with ENSPRYNG [see Warnings and Precautions (5.2)].

Caution should be exercised when considering initiation of ENSPRYNG treatment in patients whose aspartate aminotransferase (AST) or alanine aminotransferase (ALT) levels are greater than 1.5 times the upper limit of normal (ULN).

Vaccinations

Because vaccination with live-attenuated or live vaccines is not recommended during treatment with ENSPRYNG, administer all immunizations according to immunization guidelines at least 4 weeks prior to initiation of ENSPRYNG for live or live-attenuated vaccines and, whenever possible, at least 2 weeks prior to initiation of ENSPRYNG for non-live vaccines [see Warnings and Precautions (5.1)].

2.2 Recommended Dosage

For subcutaneous use only.

Prior to every use of ENSPRYNG, advise patients to consult with their healthcare professional (HCP) if they suspect an active infection, including localized infections. In case of active infection, delay use of ENSPRYNG until the infection is resolved [see Warnings and Precautions (5.1)].

The recommended loading dosage of ENSPRYNG for the first three administrations is 120 mg by subcutaneous injection at Weeks 0, 2, and 4, followed by a maintenance dosage of 120 mg every 4 weeks.

Missed Dose

If a dose of ENSPRYNG is missed for any reason other than increases in liver enzymes [see Dosage and Administration (2.4)], administer as described in Table 1.

Table 1 Recommended Dosage for Delayed or Missed Doses
Last Dose Administered | Recommended Dosage for Delayed or Missed Doses
Less than 8 weeks during the maintenance period or missed a loading dose | Administer 120 mg by subcutaneous injection as soon as possible, and do not wait until the next planned dose. Maintenance period After the delayed or missed dose is administered, reset the dose schedule to every 4 weeks. Loading period If the second loading dose is delayed or missed, administer as soon as possible and administer the 3rd and final loading dose 2 weeks later. If the third loading dose is delayed or missed, administer as soon as possible and administer the 1st maintenance dose 4 weeks later.
8 weeks to less than 12 weeks | 120 mg by subcutaneous injection at 0 ["0 weeks" refers to time of the first administration after the missed dose.] and 2 weeks, followed by 120 mg every 4 weeks.
12 weeks or longer | 120 mg by subcutaneous injection at 0, 2, and 4 weeks followed by 120 mg every 4 weeks.

2.3 Important Administration Instructions

- ENSPRYNG is intended for patient self-administration by subcutaneous injection under the guidance of a health care professional (HCP). After proper training in subcutaneous injection technique, a patient may self-inject ENSPRYNG or the patient's caregiver may administer ENSPRYNG, if the HCP determines that it is appropriate. See ENSPRYNG "Instructions for Use" (IFU) for more detailed instructions on the preparation and administration of ENSPRYNG.
- Patients or caregivers should seek immediate medical attention if the patient develops symptoms of a serious allergic reaction and should not administer further doses until evaluated by a HCP [see Contraindications (4) and Warning and Precautions (5.4)].
- Prior to use, remove the prefilled syringe from the refrigerator and allow to sit at room temperature outside of the carton for 30 minutes. Do not warm ENSPRYNG in any other way.
- Inspect visually for particulate matter and discoloration prior to administration. ENSPRYNG solution should be clear and colorless to slightly yellow. Do not use ENSPRYNG if the solution is cloudy, discolored, or contains particles, or if any part of the prefilled syringe appears to be damaged.
- Instruct patients to inject the full amount in the syringe (1 mL), which provides 120 mg of ENSPRYNG, according to the directions provided in the IFU.
- Administer ENSPRYNG by subcutaneous injection in the abdomen or thigh. Rotate injection sites with each administration. Do not give injection into moles, scars, or areas where the skin is tender, bruised, red, hard, or not intact.

2.4 Safety Monitoring During Treatment

Liver Transaminases

Monitor ALT and AST levels every 4 weeks for the first 3 months of treatment with ENSPRYNG, followed by every 3 months for one year, and thereafter as clinically necessary [see Warnings and Precautions (5.2)].

If an ALT or AST elevation of greater than 5 times the ULN occurs, discontinue ENSPRYNG as follows:

- If associated with any bilirubin elevation, discontinue ENSPRYNG, and reinitiation is not recommended.
- If not associated with any bilirubin elevation above the ULN, when the ALT or AST level has returned to the normal range and following a benefit-risk assessment of the patient, treatment with ENSPRYNG can be restarted per the schedule in Table 2.
  Table 2 Recommended Dosage for Restart of Treatment After Liver Transaminase Elevation
  Last Dose Administered | Recommended Dosage for Restart of Treatment
  Less than 12 weeks | Restart at a dosage of 120 mg by subcutaneous injection every 4 weeks.
  12 weeks or longer | Restart at a dose of 120 mg by subcutaneous injection at Weeks 0 ["0 weeks" refers to time of the first administration after the missed dose.] , 2, and 4, followed by a dosage of 120 mg every 4 weeks.
  If treatment is restarted, the liver parameters must be closely monitored, and if any subsequent increase in ALT/AST and/or bilirubin above the ULN is observed, ENSPRYNG should be discontinued, and another reinitiation is not recommended.

Neutrophil Counts

Monitor neutrophils 4 to 8 weeks after initiation of therapy and thereafter at regular clinically determined intervals. If the neutrophil count is below 1.0 × 10^9/L and confirmed by repeat testing, ENSPRYNG should be interrupted until the neutrophil count is > 1.0 × 10^9/L [see Warnings and Precautions (5.3)].

3 DOSAGE FORMS AND STRENGTHS

Injection: 120 mg/mL clear, and colorless to slightly yellow solution in single-dose prefilled syringe.

4 CONTRAINDICATIONS

ENSPRYNG is contraindicated in patients with:

- A known hypersensitivity to satralizumab or any of the inactive ingredients [see Warnings and Precautions (5.4)]
- Active Hepatitis B infection [see Warnings and Precautions (5.1)]
- Active or untreated latent tuberculosis [see Warnings and Precautions (5.1)]

5 WARNINGS AND PRECAUTIONS

5.1 Infections

An increased risk of infections, including serious and potentially fatal infections, has been observed in patients treated with IL-6 receptor antagonists, including ENSPRYNG.

The most common infections reported in a randomized clinical trial of patients treated with ENSPRYNG who were not on other chronic immunosuppressant therapies (Study 1), and that occurred more often than in patients receiving placebo, were nasopharyngitis (12%) and cellulitis (10%). The most common infections in patients who were on an additional concurrent immunosuppressant, and that occurred more often than in patients receiving placebo, were nasopharyngitis (31%), upper respiratory infection (19%), and pharyngitis (12%).

Delay ENSPRYNG administration in patients with an active infection, including localized infections, until the infection is resolved.

Hepatitis B Virus (HBV) Reactivation

Risk of HBV reactivation has been observed with other immunosuppressant therapies. Patients with chronic HBV infection were excluded from clinical trials. Perform HBV screening in all patients before initiation of treatment with ENSPRYNG. Do not administer ENSPRYNG to patients with active hepatitis. For patients who are chronic carriers of HBV [HBsAg+] or are negative for HBsAg and positive for HB core antibody [HBcAb+], consult liver disease experts before starting and during treatment with ENSPRYNG.

Tuberculosis

Tuberculosis has occurred in patients treated with other interleukin-6 receptor antagonists. Patients should be evaluated for tuberculosis risk factors and tested for latent infection prior to initiating ENSPRYNG. Consider anti-tuberculosis therapy prior to initiation of ENSPRYNG in patients with a history of latent or active tuberculosis in whom an adequate course of treatment cannot be confirmed, and for patients with a negative test for latent tuberculosis but having risk factors for tuberculosis infection. Consult infectious disease experts regarding whether initiating anti-tuberculosis therapy is appropriate before starting treatment. Patients should be monitored for the development of symptoms and signs of tuberculosis with ENSPRYNG, even if initial tuberculosis testing is negative.

Vaccinations

Live or live-attenuated vaccines should not be given concurrently with ENSPRYNG because clinical safety has not been established. Administer all immunizations according to immunization guidelines at least 4 weeks prior to initiation of ENSPRYNG for live or live-attenuated vaccines and, whenever possible, at least 2 weeks prior to initiation of ENSPRYNG for non-live vaccines.

5.2 Elevated Liver Enzymes

Mild and moderate elevations of liver enzymes have been observed in patients treated with ENSPRYNG at a higher incidence than in patients receiving placebo [see Adverse Reactions (6.1)].

ALT and AST levels should be monitored every 4 weeks for the first 3 months of treatment, followed by every 3 months for one year, and thereafter, as clinically indicated [see Dosage and Administration (2.4)].

5.3 Decreased Neutrophil Counts

Decreases in neutrophil counts were observed in patients treated with ENSPRYNG at a higher incidence than placebo [see Adverse Reactions (6.1)].

Neutrophil counts should be monitored 4 to 8 weeks after initiation of therapy, and thereafter at regular clinically determined intervals [see Dosage and Administration (2.4)].

5.4 Hypersensitivity Reactions

Hypersensitivity reactions, including rash, urticaria, and fatal anaphylaxis, have occurred with other interleukin-6 receptor antagonists.

6 ADVERSE REACTIONS

The following clinically significant adverse reactions are described elsewhere in the labeling:

- Infections [see Warnings and Precautions (5.1)]
- Elevated Liver Enzymes [see Warnings and Precautions (5.2)]
- Decreased Neutrophil Counts [see Warnings and Precautions (5.3)]
- Hypersensitivity Reactions [see Warnings and Precautions (5.4)]

6.1 Clinical Trials Experience

Because clinical studies are conducted under widely varying conditions, adverse reaction rates observed in the clinical studies of a drug cannot be directly compared to rates in the clinical studies of another drug and may not reflect the rates observed in clinical practice.

The safety of ENSPRYNG was evaluated in two randomized, placebo-controlled clinical trials [Study 1 evaluated ENSPRYNG without concurrent immunosuppressive therapy (IST) and Study 2 evaluated ENSPRYNG with concurrent IST], which included 41 anti-AQP4 seropositive patients treated with ENSPRYNG in Study 1 and 26 anti-AQP4 seropositive patients treated with ENSPRYNG in Study 2 [see Clinical Studies (14)]. In the double-blind, controlled period, the median exposure time on ENSPRYNG treatment was approximately 2 years in Study 1 and approximately 3 years in Study 2. The median exposure time on placebo treatment was approximately 1 year in both Study 1 and Study 2.

Adverse reactions that occurred in Study 1 and Study 2 in more than 5% of patients treated with ENSPRYNG, and at a greater incidence than in patients who received placebo, are shown in Table 3 and Table 4, respectively. The most common adverse reactions (15% or greater with ENSPRYNG in either) were nasopharyngitis, headache, upper respiratory tract infection, gastritis, rash, arthralgia, extremity pain, fatigue, and nausea.

Table 3 Adverse Reactions Occurring in 4 or More Patients Treated with ENSPRYNG and Greater Incidence than Placebo in Study 1
Adverse Reaction | ENSPRYNG (N = 41) % | PLACEBO (N = 23) %
Rash | 17 | 0
Arthralgia | 17 | 0
Pain in extremity | 15 | 9
Fatigue | 15 | 4
Nausea | 15 | 9
Nasopharyngitis | 12 | 4
Pruritus | 10 | 0
Depression | 10 | 0
Cellulitis | 10 | 0
Neutropenia | 10 | 4
Blood creatine phosphokinase increased | 10 | 4
Fall | 10 | 4

Table 4 Adverse Reactions Occurring in 3 or More Patients Treated with ENSPRYNG and Greater Incidence than Placebo in Study 2
Adverse Reaction | ENSPRYNG + IST (N = 26) % | PLACEBO + IST (N = 26) %
Nasopharyngitis | 31 | 15
Headache | 27 | 12
Upper respiratory tract infection | 19 | 12
Gastritis | 15 | 0
Arthralgia | 12 | 0
Pharyngitis | 12 | 8

Injection-Related Reactions

In Study 1 and Study 2, injection-related reactions were reported in 9% of patients treated with ENSPRYNG compared with 8% in patients receiving placebo. These reactions in the ENSPRYNG-treated patients were predominantly mild to moderate in severity, and most occurred within 24 hours after the injection. The most commonly reported systemic symptom was diarrhea. The reported local injection site reactions were pruritus, injection site reaction, and skin mass.

Infections

In Study 1, the rate of patients with infections was 51 patients/100 patient-years (95% CI: 32, 78) in patients treated with ENSPRYNG compared with 108 patients/100 patient-years (95% CI: 52, 199) in patients receiving placebo. The rate of patients with serious infections was 5 patients/100 patient-years (95% CI: 1, 14) in patients treated with ENSPRYNG compared with 4 patients/100 patient-years (95% CI: 0, 21) in patients receiving placebo.

In Study 2, the rate of patients with infections was 168 patients/100 patient-years (95% CI: 100, 265) in patients treated with ENSPRYNG compared with 143 patients/100 patient-years (95% CI: 83, 229) in patients treated with placebo. The rate of patients with serious infections was 4 patients/100 patient-years (95% CI: 1, 15) in patients treated with ENSPRYNG compared with 10 patients/100 patient-years (95% CI: 2, 28) in patients receiving placebo.

Laboratory Abnormalities

Decreased Neutrophil Count

Of the patients treated with ENSPRYNG, 10% had neutrophils below 1 × 10^9/L compared to 9% in placebo in Study 1. In Study 2, 15% patients had neutrophils below 1 × 10^9/L compared to 4% in placebo. There was one patient in Study 1 treated with ENSPRYNG with neutrophil counts < 0.5 × 10^9/L, and one patient in Study 2 discontinued ENSPRYNG because of neutropenia.

Decreased Platelet Count

In Study 1, a shift in platelet count decreases from normal at baseline to below the lower limit of normal (LLN) occurred in 26% of patients treated with ENSPRYNG compared to 5% of patients receiving placebo. In Study 2, decreases in platelet counts from normal at baseline to below the LLN occurred in 35% of patients treated with ENSPRYNG and in 17% of patients receiving placebo. None of the patients had a decrease in platelet count to less than 50 × 10^9/L.

Elevated Liver Enzymes

In Study 1, increases from normal at baseline to above ULN in ALT or AST occurred in 43% and 25% of patients treated with ENSPRYNG, respectively, compared to 13% and 9% of patients receiving placebo. In Study 2, increases from normal at baseline to above the ULN in ALT or AST occurred in 8% and 8% of patients treated with ENSPRYNG, respectively, compared to 12% and 19% of patients receiving placebo.

In Study 1 and Study 2 combined, elevations of ALT or AST greater than 3 times the ULN occurred in 3% of patients treated with ENSPRYNG, compared to no patients treated with placebo. These elevations were not associated with increases in total bilirubin. One patient receiving ENSPRYNG in Study 2 had an elevation of ALT above 5 times the ULN, which was observed 4 weeks after initiation of therapy, normalizing 78 days after discontinuation of ENSPRYNG.

Lipid Abnormalities

In Study 1 and Study 2, elevations in total cholesterol above 7.75 mmol/L (300 mg/dl) occurred in 12% and 15% of patients treated with ENSPRYNG, respectively, compared to no patients receiving placebo.

Elevations in triglycerides above 3.42 mmol/L (300 mg/dl) occurred in 27% and 12% of patients treated with ENSPRYNG in Study 1 and Study 2, respectively, compared to 13% and 8% of patients receiving placebo.

Fibrinogen Levels

In Study 1, the median percent reduction in fibrinogen was 38% in patients treated with ENSPRYNG compared to 5% in patients receiving placebo. In Study 2, the median percent reduction in fibrinogen level was 33% in patients treated with ENSPRYNG compared to 0% in patients receiving placebo.

Complement Levels

In Study 1, the median percent reduction in the C3 and C4 components of complement was 23% and 50% in patients treated with ENSPRYNG, respectively, compared to 0% and 1% patients receiving placebo. In Study 2, the median percent reduction in the C3 and C4 components of complement was 20% and 53% in patients treated with ENSPRYNG, respectively, compared to 0% and 1% in patients receiving placebo.

Body Weight

In the pool of Studies 1 and 2, body weight increases of at least 7% from baseline occurred in 28% of patients treated with ENSPRYNG compared to 8% of patients receiving placebo.

Body weight increases of at least 15% from baseline occurred in 4% of patients treated with ENSPRYNG compared to 4% of patients receiving placebo.

6.2 Immunogenicity

As with all therapeutic proteins, there is a potential for immunogenicity. The detection of antibody formation is highly dependent on the sensitivity and specificity of the assay. Additionally, the observed incidence of antibody (including neutralizing antibody) positivity in an assay may be influenced by several factors, including assay methodology, sample handling, timing of sample collection, concomitant medications, and underlying disease. For these reasons, comparison of the incidence of anti-satralizumab-mwge antibodies in the studies described below with the incidence of antibodies in other studies or to other products may be misleading.

In Study 1 and Study 2, anti-drug-antibodies (ADAs) were observed in 73% and 38% of patients receiving ENSPRYNG in the double-blind period, respectively. The ability of these ADAs to neutralize satralizumab-mwge binding is unknown. Patients with higher body weight and lower exposure were more likely to develop ADAs (irrespective of treatment with IST). Exposure was lower in ADA positive patients. Although anti-satralizumab-mwge antibody development was not found to affect the efficacy of ENSPRYNG in these patients, the available data are too limited to make definitive conclusions. Immunogenicity does not have a clinically-relevant impact on safety. Based on the available information, neither dose interruption nor modification is warranted in those patients who develop ADAs.

8 USE IN SPECIFIC POPULATIONS

8.1 Pregnancy

Pregnancy Exposure Registry

There is a pregnancy exposure registry that monitors pregnancy outcomes in women exposed to ENSPRYNG during pregnancy. Healthcare providers are encouraged to register patients and pregnant women are encouraged to register themselves by calling 1-833-277-9338.

Risk Summary

There are no adequate data on the developmental risk associated with the use of ENSPRYNG in pregnant women. In an animal reproduction study, no adverse effects on maternal animals or fetal development were observed in pregnant monkeys and their offspring, with administration of satralizumab-mwge at doses up to 50 mg/kg/week (see Data).

In the U.S. general population, the estimated background risk of major birth defect and miscarriage in clinically recognized pregnancies is 2 – 4% and 15 – 20%, respectively. The estimated background risk of major birth defects and miscarriage for the indicated population is unknown.

Clinical Considerations

Fetal/neonatal adverse reactions

Monoclonal antibodies are increasingly transported across the placenta as pregnancy progresses, with the largest amount transferred during the third trimester. Risks and benefits should be considered prior to administering live or live-attenuated vaccines to infants exposed to ENSPRYNG in utero [see Warnings and Precautions (5.1)].

Data

Animal Data

Weekly subcutaneous administration of satralizumab-mwge (0, 2, or 50 mg/kg) to monkeys throughout pregnancy resulted in no adverse effects on postnatal development of the offspring; however, immune function was impaired in offspring at both doses. Plasma exposures (Cave) in dams at the low and high doses were approximately 3 and 100 times, respectively, that in humans at the recommended monthly maintenance dose of 120 mg.

8.2 Lactation

Risk Summary

No information is available on the presence of satralizumab-mwge in human milk, the effects of the satralizumab-mwge on the breastfed infant, or the effects of the satralizumab-mwge on milk production. Satralizumab-mwge was excreted in the milk of lactating monkeys administered satralizumab-mwge throughout pregnancy. Human IgG is excreted in human milk and the potential for absorption in the infant is unknown. The developmental and health benefits of breastfeeding should be considered along with the mother's clinical need for ENSPRYNG and any potential adverse effects on the breastfed infant from ENSPRYNG or from the underlying maternal condition.

8.4 Pediatric Use

Safety and effectiveness in pediatric patients have not been established.

8.5 Geriatric Use

Clinical studies of ENSPRYNG did not include sufficient numbers of patients aged 65 years and older to determine whether they respond differently from younger patients. However, population pharmacokinetic analyses in patients with NMOSD did not show that age affected the pharmacokinetics of satralizumab-mwge [see Clinical Pharmacology (12.3)]. In general, caution should be used when dosing the elderly, reflecting the greater frequency of decreased hepatic, renal, or cardiac function, and of concomitant diseases or other drug therapy.

11 DESCRIPTION

Satralizumab-mwge is a recombinant humanized anti-human interleukin 6 (IL-6) receptor monoclonal antibody based on a human IgG2 framework. Each light chain and heavy chain consists of 214 and 443 amino acids, respectively. Satralizumab-mwge is a glycoprotein with an approximate molecular weight of 143 kDa and is produced by recombinant DNA technology in Chinese hamster ovary cells. The binding of satralizumab-mwge to the IL-6 receptor is pH-sensitive.

ENSPRYNG (satralizumab-mwge) injection for subcutaneous administration is supplied as a sterile, clear, colorless to slightly yellow solution with no preservative with an approximate pH of 6. ENSPRYNG is supplied in a single-dose prefilled syringe. Each syringe delivers 1 mL of solution containing 120 mg of satralizumab-mwge, L-arginine (26.1 mg), L-histidine (3.1 mg), poloxamer 188 (0.5 mg), L-aspartic acid (pH adjustment), and Water for Injection, USP.

12 CLINICAL PHARMACOLOGY

12.1 Mechanism of Action

The precise mechanism by which satralizumab-mwge exerts therapeutic effects in NMOSD is unknown but is presumed to involve inhibition of IL-6-mediated signaling through binding to soluble and membrane-bound IL-6 receptors.

12.2 Pharmacodynamics

The relationship between any of the pharmacodynamic effects of ENSPRYNG and clinical outcomes in NMOSD is unknown.

12.3 Pharmacokinetics

The pharmacokinetics of ENSPRYNG have been characterized both in Japanese and Caucasian healthy volunteers, and in NMOSD patients. The pharmacokinetics in NMOSD patients using the recommended dose were characterized using population pharmacokinetic analysis methods based on a database of 154 patients.

The concentration-time course of ENSPRYNG in patients with NMOSD was accurately described by a two-compartment population pharmacokinetic model with parallel linear and target-mediated (Michaelis-Menten) elimination and first-order subcutaneous absorption. ENSPRYNG clearance and volume parameters allometrically scaled by body weight (through power function with the fixed power coefficient of 0.75 and 1 for clearance and volume parameters, respectively). Body weight was shown to be a significant covariate, with clearance and Vc for patients weighing 123 kg (97.5th percentile of the weight distribution) increased by 71.3% and 105%, respectively, compared to a patient weighing 60 kg.

Steady state pharmacokinetics were achieved after the loading period (8 weeks) as follows [mean (±SD)]: Cmin: 19.7 (12.2) mcg/mL, Cmax: 31.5 (14.9) mcg/mL, and AUC: 737 (386) mcg.mL/day.

Absorption

The bioavailability of satralizumab-mwge was 85%.

Distribution

Satralizumab-mwge undergoes biphasic distribution. The central volume of distribution was 3.46 L and the peripheral volume of distribution was 2.07 L. The inter-compartmental clearance was 0.336 L/day.

Elimination

The total clearance of satralizumab-mwge is concentration-dependent. Linear clearance (accounting for approximately half of the total clearance at steady state using the recommended dose in NMOSD patients) is estimated to be 0.0601 L/day. The associated terminal t1/2 is approximately 30 days (range 22 – 37 days) based on data pooled from Study 1 and Study 2.

Metabolism

The metabolism of satralizumab-mwge has not been directly studied, as antibodies are cleared principally by catabolism.

Excretion

Monoclonal antibodies, including satralizumab-mwge, are not eliminated via renal or hepatic pathways.

Specific Populations

Population pharmacokinetic analyses in patients with NMOSD showed that age, gender, and race did not meaningfully influence the pharmacokinetics of satralizumab-mwge.

Patients with Renal or Hepatic Impairment

No formal studies of the effect of renal impairment or hepatic impairment on the pharmacokinetics of satralizumab-mwge were conducted.

Drug Interaction Studies

No formal drug-drug interaction studies have been performed with ENSPRYNG.

Based on population pharmacokinetic analyses of the available data, the impact of commonly used small molecule drugs on the pharmacokinetics of satralizumab-mwge remains inconclusive.

Suppression of IL-6 signaling by treatment with ENSPRYNG, from the low baseline levels seen in Study 1 and Study 2, is expected to have a minor impact on exposure of concomitant medications metabolized by CYP450 enzymes. The clinical significance of this is unknown.

13 NONCLINICAL TOXICOLOGY

13.1 Carcinogenesis, Mutagenesis, Impairment of Fertility

Carcinogenesis

Carcinogenicity studies of satralizumab-mwge were not conducted.

Mutagenesis

Genetic toxicology studies of satralizumab-mwge were not conducted. As an antibody, satralizumab-mwge is not expected to interact directly with DNA.

Impairment of Fertility

In monkeys administered satralizumab-mwge (0, 2, 10, or 50 mg/kg) weekly by subcutaneous injection for 26 weeks, no effects on sperm, estrus cycle, or male and female reproductive organs were observed. At the high dose, plasma exposures (Cave) were approximately 100 times that in humans at the recommended monthly maintenance dose of 120 mg.

14 CLINICAL STUDIES

The efficacy of ENSPRYNG for the treatment of NMOSD in adult patients was established in two studies. Study 1 was a randomized (2:1), placebo-controlled trial in 95 patients without concurrent IST (Study 1, NCT02073279) in which 64 patients were anti-AQP4 antibody positive and 31 patients were anti-AQP4 antibody negative.

Study 2 was a randomized (1:1), placebo-controlled trial in 76 adult patients with concurrent IST (Study 2, NCT02028884). Of these, 52 adult patients were anti-AQP4 antibody positive and 24 adult patients were anti-AQP4 antibody negative.

Patients met the following eligibility criteria:

1. Study 1: Clinical evidence of 1 relapse in the previous 12 months
2. Study 2: Clinical evidence of at least 2 relapses in the previous 2 years, at least one of which must have occurred in the previous year
3. EDSS score of 0 to 6.5 (both studies)
4. Study 1: Patients were excluded if previously treated with IST within an interval specified for each such therapy
5. Study 2: One of the following baseline treatments at a stable dose as a monotherapy for 8 weeks prior to baseline: azathioprine, mycophenolate mofetil, oral corticosteroids

In Study 1, 41 anti-AQP4 antibody positive adult patients were randomized to and received ENSPRYNG and 23 received placebo. Females accounted for 76% of the ENSPRYNG group and 96% of the placebo group. The remaining baseline demographic characteristics were balanced between the treatment groups. The mean age was 44 years. Fifty percent were White, 22% were Black or African-American, and 20% were Asian. The mean EDSS score was 3.8.

In Study 2, 26 anti-AQP4 antibody positive adult patients were randomized to and received ENSPRYNG and 26 received placebo. All patients were receiving either concurrent azathioprine (42%), oral corticosteroids (52%), or mycophenolate mofetil (6%) during the trial. The baseline demographic and disease characteristics were balanced between the treatment groups. Females accounted for 100% of the study population. Forty-six percent of patients were White and 52% were Asian. The mean age was 46 years. The mean EDSS score was 4.0.

All potential relapses were adjudicated by a blinded Clinical Endpoint Committee (CEC). The primary efficacy endpoint for both studies was the time to the first CEC-confirmed relapse.

In Study 1, the time to the first CEC-confirmed relapse was significantly longer in ENSPRYNG-treated patients compared to patients who received placebo (risk reduction 55%; hazard ratio 0.45; p = 0.0184). In the anti-AQP4 antibody positive population, there was a 74% risk reduction; hazard ratio 0.26; p = 0.0014 (Table 5; Figure 1). There was no evidence of a benefit in the anti-AQP4 antibody negative patients.

In Study 2, the time to the first CEC-confirmed relapse was significantly longer in patients treated with ENSPRYNG compared to patients who received placebo (risk reduction 62%; hazard ratio 0.38; p = 0.0184). In the anti-AQP4 antibody positive population, there was a 78% risk reduction; hazard ratio 0.22; p = 0.0143 (Table 5; Figure 2). There was no evidence of a benefit in the anti-AQP4 antibody negative patients.

Table 5 Efficacy Results from Study 1 and Study 2 in anti-AQP4 Antibody Positive NMOSD Patients
 | Study 1 |  | Study 2
 | ENSPRYNG N=41 | Placebo N=23 | ENSPRYNG + IST [IST = immunosuppressant therapy] N= 26 | Placebo + IST N=26
Time to Clinical Endpoint Committee (CEC)-Determined Relapse (Primary Efficacy Endpoint)
Number (%) of Patients with Relapse | 9 (22) | 13 (56.5) | 3 (11.5) | 11 (42.3)
Hazard Ratio (95% CI) | 0.26 (0.11, 0.63) |  | 0.22 (0.06, 0.82)
p-value | 0.0014 |  | 0.0143
Risk Reduction | 74% |  | 78%
Proportion of Protocol Defined Relapse-Free Patients at 96 Weeks | 76.5% | 41.1% | 91.1% | 56.8%

Figure 1 Study 1: Time to First CEC-Determined NMOSD Relapse in the Randomized Controlled Period in the ITT Population Anti-AQP4 Antibody Positive Patients

Figure 2 Study 2: Time to First CEC-Determined NMOSD Relapse in the Randomized Controlled Period in the ITT Population Anti-AQP4 Antibody Positive Patients

16 HOW SUPPLIED/STORAGE AND HANDLING

16.1 How Supplied

ENSPRYNG (satralizumab-mwge) injection is available as a sterile, preservative-free, clear, colorless to slightly yellow solution in single-dose prefilled syringe (PFS) with needle safety device.

ENSPRYNG PFS is not made with natural rubber latex. Each ENSPRYNG carton contains one single-dose 120 mg/mL prefilled syringe (NDC 50242-007-01).

16.2 Storage and Handling

- Refrigerate at 2°C to 8°C (36°F to 46°F) in original carton to protect from light. Do not freeze. Do not shake.
- Prior to administration, ENSPRYNG, if unopened, can be removed from and returned to the refrigerator, if necessary. The total combined time out of refrigeration should not exceed 8 days at a temperature that does not exceed 30°C (86°F).

17 PATIENT COUNSELING INFORMATION

Advise the patients to read the FDA-approved patient labeling (Medication Guide and Instructions for Use).

Infections

Inform patients that an increased risk of infections, including serious and potentially fatal infections, has been observed in patients treated with IL-6 receptor antagonists, including ENSPRYNG. Instruct patients to contact their healthcare provider immediately when symptoms suggesting infection (e.g., fever, chills, constant cough, or sore throat) appear during treatment [see Warning and Precautions (5.1)].

Vaccinations

Advise patients to complete any required vaccinations at least 4 weeks prior to initiation of ENSPRYNG for live or live-attenuated vaccines and, whenever possible, at least 2 weeks prior to initiation of ENSPRYNG for non-live vaccines [see Warnings and Precautions 5.1].

Elevated Liver Enzymes

Inform patients on the importance of liver enzyme testing [see Warnings and Precautions (5.2)].

Decreased Neutrophil Counts

Inform patients on the importance of neutrophil count testing [see Warnings and Precautions (5.3)].

Hypersensitivity Reactions

Inform patients about the signs and symptoms of hypersensitivity reactions and anaphylaxis and advise them to contact their healthcare provider immediately if these symptoms occur [see Warnings and Precautions (5.4)].

Instruction on Injection Technique

Instruct patients and caregivers to read the Instructions for Use before the patient starts using ENSPRYNG, and each time the patient gets a refill as there may be new information they need to know.

Perform the first injection under the guidance of a qualified healthcare professional. If a patient or caregiver is to administer subcutaneous ENSPRYNG, instruct him/her in injection techniques and assess his/her ability to inject subcutaneously to ensure proper administration of subcutaneous ENSPRYNG and the suitability for home use [see Dosage and Administration (2.3) and Instructions for Use].

Instruct patients to remove the prefilled syringe from the refrigerator prior to use and allow to sit at room temperature outside of the carton for 30 minutes. Do not warm ENSPRYNG in any other way.

Advise patients to consult their healthcare provider if the full dose is not received.

A puncture-resistant container for disposal of syringes should be used and should be kept out of the reach of children. Instruct patients or caregivers in the technique as well as proper prefilled syringe disposal, and caution against reuse of these items.

Pregnancy Exposure Registry

Encourage patients to enroll in the ENSPRYNG Pregnancy Registry if they become pregnant while taking ENSPRYNG. The Registry monitors fetal outcomes of pregnant women exposed to ENSPRYNG [see Use in Specific Populations (8.1)].

ENSPRYNG® [satralizumab-mwge]

Manufactured by:
Genentech, Inc.
A Member of the Roche Group
1 DNA Way
South San Francisco, CA 94080-4990

ENSPRYNG® is a registered trademark of
Chugai Pharmaceutical Co., Ltd., Tokyo, Japan
©2022 Genentech, Inc. All rights reserved.

U.S. License No.: 1048

MEDICATION GUIDE
ENSPRYNG® (en-spryng)
(satralizumab-mwge)
injection, for subcutaneous use

What is the most important information I should know about ENSPRYNG?
ENSPRYNG may cause serious side effects including:

1. Infections. ENSPRYNG can increase your risk of serious infections some of which can be life-threatening. Talk to your healthcare provider if you are being treated for an infection or call them right away if you think you have signs of an infection, with or without a fever, such as:
  - chills, feeling tired, muscle aches, cough that will not go away or a sore throat
  - skin redness, swelling, tenderness, pain or sores on your body
  - diarrhea, belly pain, or feeling sick
  - burning when you urinate or urinating more often than usual
  Your healthcare provider will check if you have an infection and treat it if needed before you start or continue to take ENSPRYNG.

- Your healthcare provider should test you for hepatitis and tuberculosis (TB) before you start taking ENSPRYNG.
- All required vaccinations should be completed before starting ENSPRYNG. People using ENSPRYNG should not be given 'live' or 'live-attenuated' vaccines. 'Live' or 'live-attenuated' vaccines should be given at least 4 weeks before you start ENSPRYNG. Your healthcare provider may recommend that you get a 'non-live' (inactivated) vaccine, such as some of the seasonal flu vaccines. If you plan to get a 'non-live' (inactivated) vaccine, it should be given, whenever possible, at least 2 weeks before you start ENSPRYNG.

2. Increased liver enzymes.
  Your healthcare provider should order blood tests to check your liver enzymes before and while you are taking ENSPRYNG. Your healthcare provider will tell you how often you will need to have these blood tests. Make sure you get all of your follow-up blood tests as ordered by your healthcare provider. Your healthcare provider will tell you if you need to wait to start ENSPRYNG if your liver enzymes are increased.
3. Low neutrophil count.
  ENSPRYNG can cause a decrease in your neutrophil counts in your blood. Neutrophils are white blood cells that help the body fight off bacterial infections. Your healthcare provider should order blood tests to check your neutrophil count while you are taking ENSPRYNG.

See "What are the possible side effects with ENSPRYNG?"

What is ENSPRYNG?
ENSPRYNG is a prescription medicine used to treat neuromyelitis optica spectrum disorder (NMOSD) in adults who are aquaporin-4 (AQP4) antibody positive.
It is not known if ENSPRYNG is safe and effective in children.

Do not take ENSPRYNG if you:

- are allergic to satralizumab-mwge or any of the ingredients in ENSPRYNG. See "What are the ingredients in ENSPRYNG?" at the end of this Medication Guide for a complete list of ingredients in ENSPRYNG.
- have an active hepatitis B infection.
- have active or untreated inactive (latent) TB.

Before you take ENSPRYNG, tell your healthcare provider about all of your medical conditions, including if you:

- have or think you have an infection. See "What is the most important information I should know about ENSPRYNG?"
- have liver problems.
- have ever had hepatitis B or are a carrier of the hepatitis B virus.
- have had or have been in contact with someone with tuberculosis.
- have had a recent vaccination or are scheduled to receive any vaccination.
- are pregnant, think that you might be pregnant, or plan to become pregnant. It is not known if ENSPRYNG will harm your unborn baby.
  - Pregnancy Registry: There is a registry for pregnant women who take ENSPRYNG. The purpose of this registry is to check the health of the pregnant mother and her baby. If you are pregnant or become pregnant while taking ENSPRYNG, talk to your healthcare provider about how you can join this pregnancy registry or you may contact the registry at 1-833-277-9338 to enroll.
- are breastfeeding or plan to breastfeed. It is not known if ENSPRYNG passes into your breast milk. Talk to your healthcare provider about the best way to feed your baby if you take ENSPRYNG.

Tell your healthcare provider about all the medicines you are taking, including prescription and over-the-counter medicines, vitamins, and herbal supplements.

How should I take ENSPRYNG?

- ENSPRYNG is provided as a solution in a single-dose, prefilled syringe of 120 mg/mL of satralizumab-mwge.
- See the Instructions for Use inside the carton for complete instructions for the right way to prepare and inject ENSPRYNG.
- ENSPRYNG is given by an injection under the skin (subcutaneously). If your healthcare provider decides that you or your caregiver can give your injections of ENSPRYNG, you or your caregiver should receive training on the right way to prepare and inject ENSPRYNG.
- Always inject all of the medicine in the syringe.
- The first 3 injections (loading period) of ENSPRYNG are taken 1 time every 2 weeks.
- After this, injection of ENSPRYNG is taken every 4 weeks (maintenance period). Keep taking ENSPRYNG 1 time every 4 weeks for as long as your healthcare provider tells you to.
- If you miss a dose of ENSPRYNG, talk to your health care provider about restarting dosing.

What are the possible side effects of ENSPRYNG?
ENSPRYNG may cause serious side effects, including:

- See "What is the most important information I should know about ENSPRYNG?"
- Serious allergic reactions. Serious allergic reactions that may be life-threatening have happened with other medicines like ENSPRYNG. Tell your healthcare provider before taking your next dose if you had hives, rash, or flushing after your injection. Seek medical attention right away if you have any symptoms of a serious allergic reaction, such as:

- shortness of breath or trouble breathing
- dizziness or feeling faint

- swelling of your lips, face, or tongue
- moderate or severe stomach (abdominal) pain or vomiting
- chest pain

- The most common side effects of ENSPRYNG include:

- sore throat, runny nose (nasopharyngitis)
- rash
- fatigue
- extremity pain

- headache
- upper respiratory tract infection
- nausea
- inflammation of the stomach lining (gastritis)
- joint pain

These are not all the possible side effects of ENSPRYNG.
Call your doctor for medical advice about side effects. You may report side effects to FDA at 1-800-FDA-1088. You may also report side effects to Genentech at 1-888-835-2555.

How should I store ENSPRYNG?

- Store ENSPRYNG in the refrigerator between 36°F to 46°F (2°C to 8°C) in the original carton.
- Protect from light.
- Do not freeze or use the syringe if it has been frozen.
- Do not shake.
- ENSPRYNG, if unopened, can be removed from and returned to the refrigerator, if needed. The total combined time out of the refrigerator should not be more than 8 days at a temperature that does not go above 86°F (30°C).

General information about the safe and effective use of ENSPRYNG.
Medicines are sometimes prescribed for purposes other than those listed in a Medication Guide. Do not use ENSPRYNG for a condition for which it was not prescribed. Do not give ENSPRYNG to other people, even if they have the same symptoms that you have. It may harm them. You can ask your pharmacist or healthcare provider for information about ENSPRYNG that is written for health professionals.

What are the ingredients in ENSPRYNG?
Active ingredient: satralizumab-mwge
Inactive ingredients: L-arginine, L-histidine, poloxamer 188, L-aspartic acid, and Water for Injection.
Manufactured by: Genentech, Inc., A Member of the Roche Group, 1 DNA Way, South San Francisco, CA 94080-4990
ENSPRYNG® is a registered trademark of Chugai Pharmaceutical Co., Ltd., Tokyo, Japan
U.S. License No.: 1048
For more information, go to www.ENSPRYNG.com or call 1-844-NSPRYNG.

This Medication Guide has been approved by the U.S. Food and Drug Administration

Issued: 3/2022

Instructions for Use ENSPRYNG® (en-spryng) (satralizumab-mwge) Injection

Read this Instructions for Use before you start using your prefilled syringe and each time you get a refill. There may be new information. This information does not take the place of talking to your healthcare provider about your medical condition or treatment. Your healthcare provider will decide if you or a caregiver can give you injections of ENSPRYNG at home. They will also show you or a caregiver the correct and safe way to use the syringe before you use it for the first time.

Talk to your healthcare provider if you have any questions.

Important Information

- Each syringe is prefilled with a medicine called ENSPRYNG.
- Each carton of ENSPRYNG contains only 1 prefilled syringe.
- Each prefilled syringe can be used only 1 time.

Do not share your ENSPRYNG syringe with other people. You may give them a serious infection or get a serious infection from them.

Do not:

- take the needle cap off until you are ready to inject ENSPRYNG.
- use the syringe if it has been dropped or damaged.
- try to take the syringe apart at any time.
- leave the syringe unattended.
- re-use the same syringe.

How should I store the ENSPRYNG prefilled syringe?

- Keep the unused syringe in the refrigerator between 36°F to 46°F (2°C to 8°C) until ready to use.
- Before giving an injection, if the ENSPRYNG is not opened, it can be removed from and placed back in the refrigerator if needed. The total combined time out of the refrigerator should not be more than 8 days at a temperature that does not go above 86°F (30°C).
- Keep the syringe in its original carton away from direct sunlight.
- Always keep the syringe dry.

Keep the ENSPRYNG syringe and all medicines out of the reach of children.

Do not:

- freeze the syringe.
- use the syringe if it has been frozen.
- shake.

Supplies needed to give your injection

Each ENSPRYNG carton contains:

- 1 prefilled syringe for 1-time use only.

Not included in the carton:

- 1 alcohol pad
- 1 sterile cotton ball or gauze
- 1 small bandage
- 1 FDA-cleared puncture-resistant sharps container for safe disposal of the needle cap and used syringe. See Step 21 "Disposing of ENSPRYNG" at the end of this Instructions for Use.

ENSPRYNG prefilled syringe
(See Figure A and Figure B)
Before use:

Figure A

After use:

Figure B

The syringe has a needle-shield that automatically covers the needle when the injection is complete.

Prepare to use ENSPRYNG

1. Take the carton containing the syringe out of the refrigerator and place it on a clean, flat work surface (like a table).
2. Check the expiration (EXP) date on the back of the carton (See Figure C). Do not use if the carton has expired.
3. Check the front of the carton to make sure it is sealed (Figure C). Do not use if the seal has been broken.

If the expiration date has passed or the seal is broken, do not use. Then go to Step 21 "Disposing of ENSPRYNG" and contact your healthcare provider.

Figure C

4. Open the sealed carton (See Figure D).

Figure D

5. Carefully lift the syringe out of the carton by holding the barrel (See Figure E).
  Do not:
  - turn the carton upside down to remove the syringe.
  - touch the activation guards because this may damage the syringe.
  - hold the plunger or needle cap.

Figure E

Check the syringe

(See Figure F)

6. Check the expiration date on the syringe. Do not use the syringe if it has expired.
7. Check the syringe for any damage. Do not use if it is cracked or broken.
8. Check that the liquid through the viewing window is clear and colorless to slightly yellow. Do not inject the medicine if the liquid is cloudy, discolored, or has particles in it.
  - There may be some small air bubbles in the syringe. This is normal and you should not try to remove them.

Figure F

If the expiration (EXP) date has passed, the syringe is damaged or the liquid is cloudy, discolored or has particles in it, do not use. Then go to Step 21 "Disposing of ENSPRYNG" and contact your healthcare provider.

Let your syringe warm up

9. After you have checked the syringe, place it on a clean, flat work surface (like a table) for 30 minutes. This will allow it to reach room temperature. (See Figure G).
  It is important to let the syringe gently warm up as injecting cold medicine may feel uncomfortable and make it harder to push.
  Do not:
  - speed up the warming process in any way, such as using a microwave or placing the syringe in warm water.
  - remove the needle cover while the syringe is reaching room temperature.

Figure G

Wash your hands

10. Wash your hands with soap and water. (See Figure H).

Figure H

Choose the injection site

11. Choose your injection site in either:
  - the lower part of your stomach (abdomen) or
  - the front and middle of your thighs. (See Figure I).
    Figure I
  - Do not inject into the 2-inch (5 cm) area around your belly button.
  - Do not inject into moles, scars, bruises, or areas where the skin is tender, red, hard or broken.

Choose a different injection site for each new injection. Choose a different place to inject which is at least 1 inch (2.5 cm) away from the place where you last injected.

Clean the injection site

12. Wipe the injection site with an alcohol pad and let it air dry.
  Do not:
  - fan or blow on the area which you have cleaned.
  - touch the injection site again before you give the injection.

Figure J

Inject ENSPRYNG

13. Hold the barrel of the syringe between your thumb and index finger. With your other hand, pull the needle cap straight off. You may see a drop of liquid at the end of the needle. This is normal and will not affect your dose (See Figure K).
  - Use the syringe within 5 minutes of removing the cap or the needle may clog.
    Do not:
  - take the needle cap off until you are ready to inject ENSPRYNG.
  - put the needle cap back on after it has been removed as this may damage the needle.
  - touch the needle or let it touch any surfaces after removing the needle cap.

Figure K

14. Throw away the needle cap in a puncture-resistant sharps container immediately. See Step 21 "Disposing of ENSPRYNG".
15. Hold the barrel of the syringe using your thumb and index finger. With your other hand, pinch the area of skin you have cleaned (See Figure L).
16. Use a quick, dart-like motion to insert the needle at an angle between 45° to 90°(See Figure L).
  Do not:
  - insert the needle through clothing.
  - change the angle of the injection.
  - insert the needle again.

Figure L

17. After the needle is inserted, let go of the pinched skin.
18. Slowly inject all of the medicine by gently pushing the plunger all the way down until it touches the activation guards (See Figure M).
  Figure M
19. Gently release the plunger and allow the needle to come out of the skin at the same angle it was inserted (See Figure N).
  Figure N
  - The needle will now be covered by the needle-shield. If the needle is not covered, carefully place the syringe into a puncture-resistant sharps container to avoid injury. See Step 21 "Disposing of ENSPRYNG".

Taking care of the injection site

20. There may be a little bleeding at the injection site. You can press a cotton ball or gauze over the injection site but do not rub it. If needed, you may also cover the area you injected with a small bandage. If the medicine gets into contact with your skin, wash the area with water.

Disposing of ENSPRYNG

21. Put your used syringe in an FDA-cleared sharps disposal container immediately after use (See Figure O). Do not throw away (dispose of) the syringe in your household trash.
  Figure O
  - If you do not have an FDA-cleared sharps disposal container, you may use a household container that is:
    - made of a heavy-duty plastic
    - can be closed with a tight-fitting, puncture-resistant lid, without sharps being able to come out
    - upright and stable during use
    - leak-resistant
    - properly labeled to warn of hazardous waste inside the container
  - When your sharps disposal container is almost full, you will need to follow your community guidelines for the right way to dispose of your sharps disposal container. There may be state or local laws about how you should throw away used needles and syringes. For more information about the safe sharps disposal, and for specific information about sharps disposal in the state that you live in, go to the FDA's website at: http://www.fda.gov/safesharpsdisposal.
  - Do not dispose of your used sharps disposal container in trash unless your community guidelines permit this.
  - Do not recycle your used sharps disposal container.

This Instructions for Use has been approved by the U.S. Food and Drug Administration.

Manufactured by:
Genentech, Inc.
A Member of the Roche Group
1 DNA Way
South San Francisco, CA 94080-4990

U.S. License No.: 1048

Approved: 8/2020

ENSPRYNG® is a registered trademark of Chugai Pharmaceutical Co., Ltd., Tokyo, Japan

© 2020 Genentech, Inc. All rights reserved.

Representative sample of labeling (see the HOW SUPPLIED section for complete listing):

PRINCIPAL DISPLAY PANEL - 120 mg/mL Syringe Carton

NDC 50242-007-01

Rx only

Enspryng®
(satralizumab-mwge)
Injection

120 mg/mL

For Subcutaneous Use.
Single-Dose Prefilled Syringe.

Refrigerate at 2°C to 8°C (36°F to 46°F) in original carton to protect from light.
Do not freeze. Do not shake.

ATTENTION PHARMACIST: Each patient is required to receive the enclosed
Medication Guide.

1 prefilled syringe

Genentech

10240933